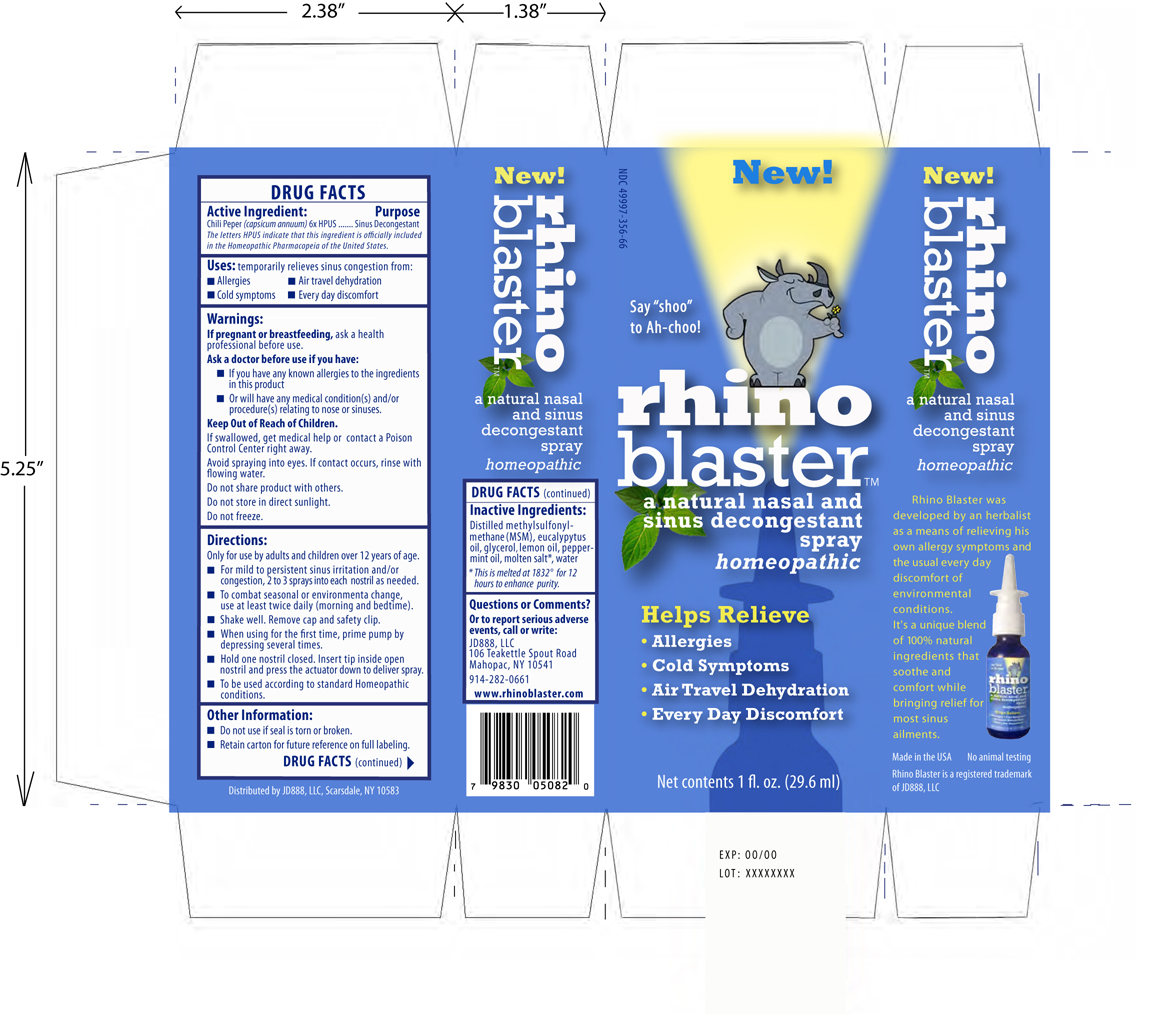 DRUG LABEL: RhinoBlaster
NDC: 49997-356 | Form: SPRAY
Manufacturer: JD888 LLC
Category: homeopathic | Type: HUMAN OTC DRUG LABEL
Date: 20100329

ACTIVE INGREDIENTS: Chili Pepper 6 [hp_X]/30 mL
INACTIVE INGREDIENTS: Peppermint Oil; Lemon Oil; Eucalyptus Oil; Sodium Chloride; Dimethyl Sulfone; Glycerin; Water

Drug Facts
Active Ingredient Purpose
Chili Pepper (capsicum annuum) 6x HPUS Sinus Decongestant
The letters HPUS indicate that this ingredient is officially included in the Homeopathic Pharmacopeia of the United States.

HOW SUPPLIED

Distributed by JD888, LLC, Scarsdale, NY 10583
Exp: 00/00
Lot: XXXXXXXX

INDICATIONS AND USAGE

Uses: temporarily relieves sinus congestion from:
Allergies, Air travel dehydration, Cold symptoms, every day discomfort

Warnings:

If pregnant or breastfeeding, ask a health professional before use.
Ask a doctor before use if you have:
If you have any known allergies to the ingredients in this product
Or will have any medical condition(s) and/or procedure(s) relating to nose or sinuses.
Keep Out of Reach of Children.
If swallowed, get medical help or contact a Poison Control Center right away.
Avoid spraying into eyes. If contact occurs, rinse with flowing water.
Do not share product with others.
Do not store in direct sunlight.
Do not freeze.

Directions:
Only for use by adults and children over 12 years of age.
For mild to persistent sinus irritation and/or congestion, 2 to 3 sprays into each nostril as needed.
To combat seasonal or environmental change, use at lease twice daily (morning and bedtime).
Shake well. Remove cap and safety clip.
When using for the first time, prime pump by depressing several times.
Hold one nostril closed. Insert tip inside open nostril and press the actuator down to deliver spray.
To be used according to standard Homeopathic conditions.

Other Information
Do not use if seal is torn or broken
Retain carton for future reference on full labeling

Inactive Ingredients

Distilled methylsulfonylmethane (MSM), eucalyptus oil, glycerol, lemon oil, peppermint oil, molten salt*, water
*This is melted at 1832 degrees for 12 hours to enhance purity.

Questions or Comments, Or to report serious adverse events, call or write:
JD888, LLC
106 Teakettle Spout Road
Mahopac, NY 10541
914-282-0661
www.rhinoblaster.com

PACKAGE LABEL

NDC 49997-356-66
New! Say "shoo" to Ah-choo!"
Rhinoblaster a natural nasal and sinus decongestant spray homeopathic
Helps relieve allergies, cold symptoms, air travel dehydration, every day discomfort
Net contents 1 fl. oz. (29.6 ml)

Rhino Blaster was developed by an herbalist as a means of relieving his own allergy symptoms and the usual every day discomfort of environmental conditions. It's a unique blend of 100% natural ingredients that soothe and comfort while bringing relief for most sinus ailments. Made in the USA. No animal testing. Rhino Blaster is a registered trademark of JD888, LLC.

Distributed by JD888, LLC, Scarsdale, NY 10583
Exp: 00/00
Lot: XXXXXXXX